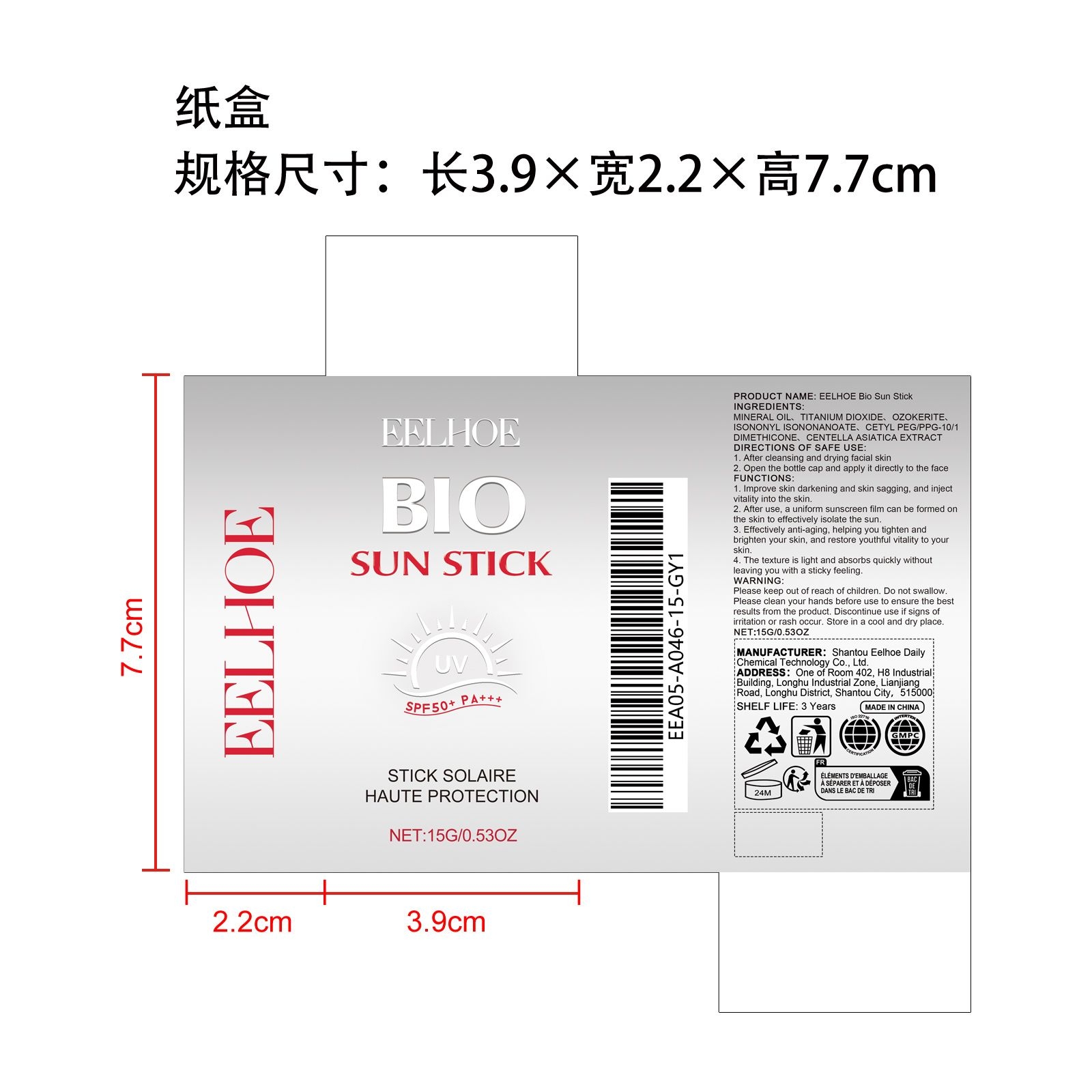 DRUG LABEL: EELHOE Bio Sun Stick
NDC: 85064-027 | Form: CREAM
Manufacturer: Shantou Eelhoe Daily Chemical Technology Co., Ltd.
Category: otc | Type: HUMAN OTC DRUG LABEL
Date: 20260114

ACTIVE INGREDIENTS: CENTELLA ASIATICA 0.015 mg/15 mg
INACTIVE INGREDIENTS: MINERAL OIL 6.21 mg/15 mg; ISONONYL ISONONANOATE 1.5 mg/15 mg; CETYL PEG/PPG-10/1 DIMETHICONE (HLB 2) 0.525 mg/15 mg; TITANIUM DIOXIDE 3.75 mg/15 mg; CERESIN 3 mg/15 mg

ACTIVE INGREDIENT

CENTELLA ASIATICA EXTRACT

PURPOSE

1. Improve skin darkening and skin sagging, and inject vitality into the skin.

2. After use, a uniform sunscreen film can be formed on the skin to effectively isolate the sun.

3. Effectively anti-aging, helping you tighten and brighten your skin, and restore youthful vitality to your skin.

4. The texture is light and absorbs quickly without leaving you with a sticky feeling.

WHEN USING

1. After cleansing and drying facial skin

2. Open the bottle cap and apply it directly to the face

WARNINGS

Please keep out of reach of children. Do not swallow.Please clean your hands before use to ensure the best results from the product. Discontinue use if signs of irritation or rash occur. Store in a cool and dry place.

DO NOT USE

Discontinue use if signs of irritation or rash occur.

STOP USE

Discontinue use if signs of irritation or rash occur.

KEEP OUT OF REACH OF CHILDREN

Please keep out of reach of children. Do not swallow.

STORAGE AND HANDLING

Store in a cool and dry place.

INACTIVE INGREDIENT

MINERAL OIL、TITANIUM DIOXIDE、OZOKERITE、ISONONYL ISONONANOATE、CETYL PEG/PPG-10/1 DIMETHICONE

INDICATIONS AND USAGE

1. After cleansing and drying facial skin

2. Open the bottle cap and apply it directly to the face

DOSAGE AND ADMINISTRATION

1. After cleansing and drying facial skin

2. Open the bottle cap and apply it directly to the face